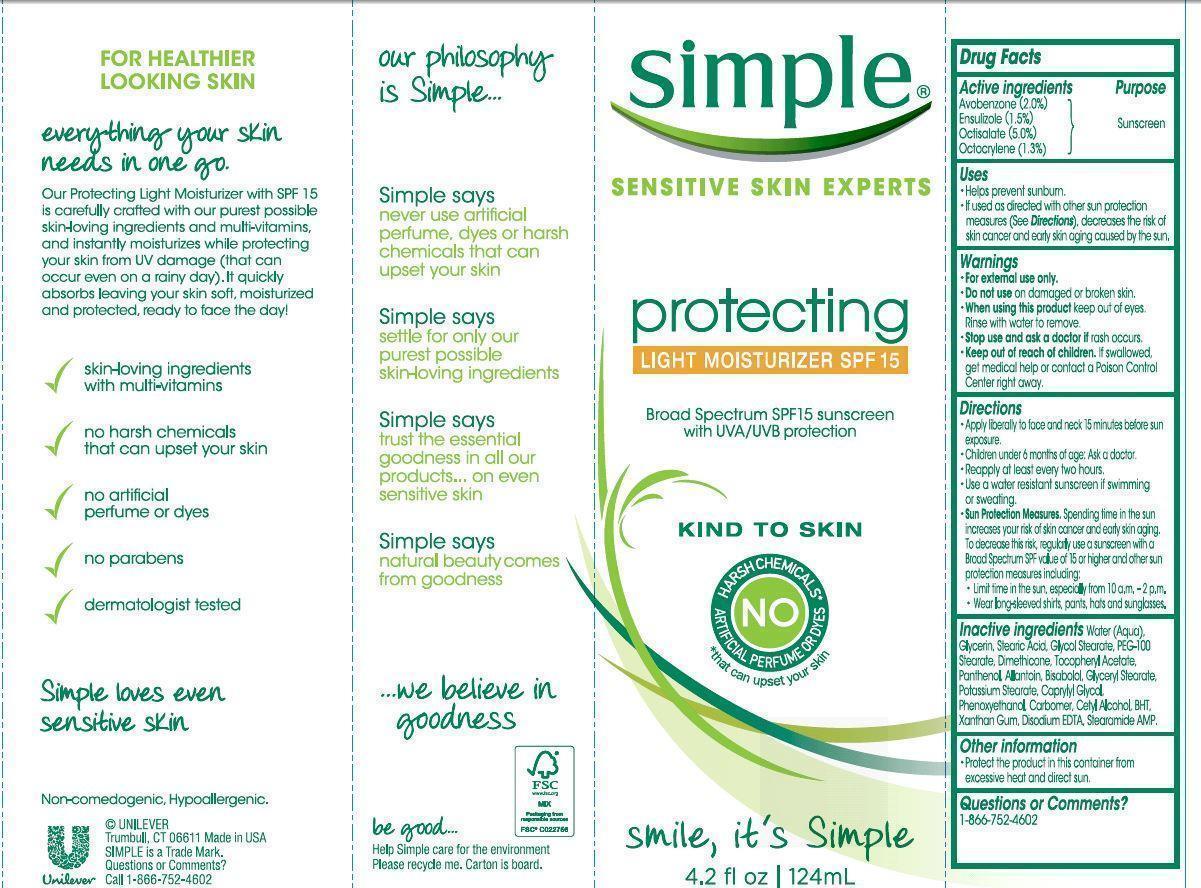 DRUG LABEL: Simple
NDC: 64942-1355 | Form: LOTION
Manufacturer: CONOPCO Inc. d/b/a Unilever
Category: otc | Type: HUMAN OTC DRUG LABEL
Date: 20241107

ACTIVE INGREDIENTS: AVOBENZONE 2 g/100 mL; ENSULIZOLE 1.5 g/100 mL; OCTISALATE 5 g/100 mL; OCTOCRYLENE 1.3 g/100 mL
INACTIVE INGREDIENTS: WATER; GLYCERIN; STEARIC ACID; GLYCOL STEARATE; PEG-100 STEARATE; DIMETHICONE; POTASSIUM STEARATE; GLYCERYL MONOSTEARATE; CAPRYLYL GLYCOL; CETYL ALCOHOL; XANTHAN GUM; STEARAMIDE AMP; .ALPHA.-TOCOPHEROL ACETATE, D-; PHENOXYETHANOL; EDETATE DISODIUM; PANTHENOL; ALLANTOIN; LEVOMENOL; BUTYLATED HYDROXYTOLUENE

Simple Light Moisturizer SPF 15

SIMPLE LIGHT MOISTURIZER SUNSCREEN SPR 15 - (avobenzone, ensulizole, octisalate, octocrylene) lotion

Simple Light Moisurizer Sunscreen SPF 15

Drug Facts

Active Ingredients
Avobenzone (2.0%)
Ensulizole (1.5%)
Octisalate (5.0%)

Octocrylene (1.3%)

Purpose

Sunscreen

Uses

· helps prevent sunburn.
· if used as directed with other sun protection measures (see Directions), decreases the risk of skin cancer and early skin aging caused by the sun.

Warnings

For external use only
Do not use on damaged or broken skin
When using this product keep out of eyes. Rinse with water to remove
Stop use and ask a doctor if rash occurs
Keep out of reach of children
If product is swallowed, get medical help or contact a Poison Control Center right away.

· When using this product keep out of eyes. Rinse with water to remove.

· Stop use and ask a doctor if rash occurs.

· Keep out of reach of children. If swallowed, get medical help or contact a Poison Control Center right away.

Directions

Apply liberally to face and neck 15 minutes before sun exposure.

· Children under 6 months: Ask a doctor.

· Reapply at least every two hours.

· Use water resistant sunscreen if swimming or sweating.

· Sun Protection Measures. Spending time in the sun increases your risk of skin cancer and early skin aging. To decrease this risk, regularly use a sunscreen with a Broad Spectrum SPF value of 15 or higher and other sun protection measures including:
· Limit time in the sun, especially from 10a.m. - 2p.m.
· Wear long-sleeved shirts, pants, hats, and sunglasses.

Inactive ingredients

Water (Aqua), Glycerin, Stearic Acid, Glycol Stearate, PEG-100 Stearate, Dimethicone, Tocopheryl Acetate, Panthenol, Allantoin, Bisabolol, Glyceryl Stearate, Potassium Stearate, Caprylyl Glycol, Phenoxyethanol, Carbomer, Cetyl Alcohol, BHT, Xanthan Gum, Disodium EDTA, Stearamide AMP.

Other information

Protect the product in this container from excessive heat and direct sun.

Questions or comments?

1-866-752-4602